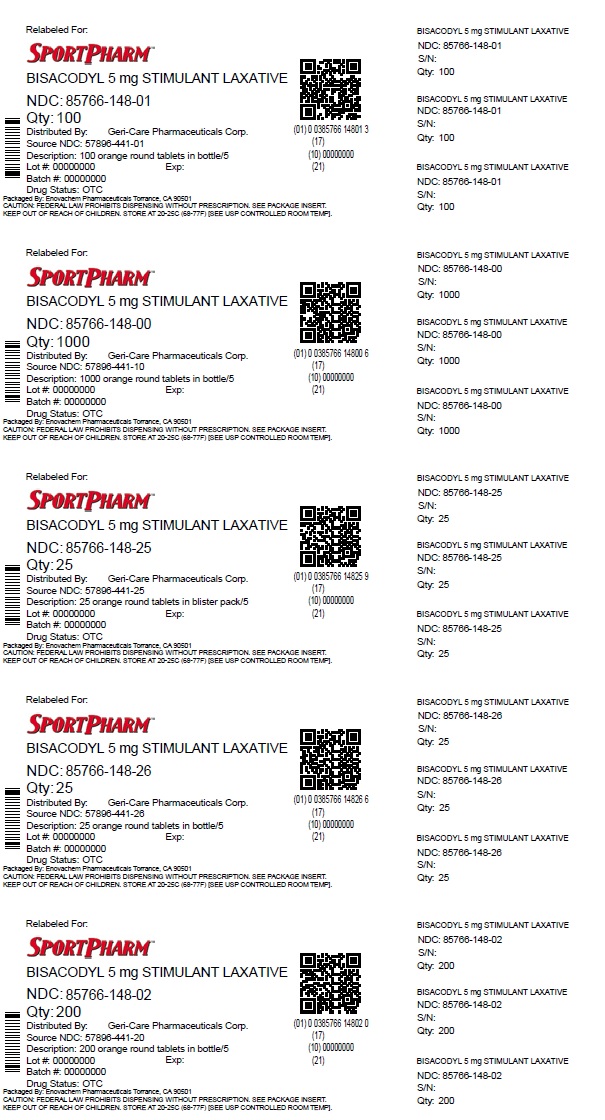 DRUG LABEL: stimulant laxative enteric coated
NDC: 85766-148 | Form: TABLET
Manufacturer: Sportpharm LLC
Category: otc | Type: HUMAN OTC DRUG LABEL
Date: 20260206

ACTIVE INGREDIENTS: BISACODYL 5 mg/1 1
INACTIVE INGREDIENTS: SODIUM ALGINATE; SODIUM BENZOATE; SODIUM BICARBONATE; STEARIC ACID; SUCROSE; TALC; TITANIUM DIOXIDE; TRIACETIN; TRIETHYL CITRATE; ACACIA; AMMONIA; CALCIUM CARBONATE; CARNAUBA WAX; STARCH, CORN; D&C YELLOW NO. 10; FD&C YELLOW NO. 6; HYPROMELLOSES; FERROSOFERRIC OXIDE; LACTOSE MONOHYDRATE; MAGNESIUM STEARATE; METHYLPARABEN; POLYDEXTROSE; POLYETHYLENE GLYCOL, UNSPECIFIED; POLYVINYL ACETATE PHTHALATE; PROPYLPARABEN; PROPYLENE GLYCOL; POVIDONE; SHELLAC; DIMETHICONE; SILICON DIOXIDE

Active ingredient (in each tablet)

Bisacodyl 5 mg

Purpose

Stimulant Laxative

Uses

- for relief of occasional constipation and irregularity
- this product generally produces bowel movement in 6 to 12 hours

Warnings

Do not useif you cannot swallow without chewing
Ask a doctor before use if you have
• stomach pain, nausea, vomiting
• noticed a sudden change in bowel habits that lasts more than 2 weeks
When using this product• do not chew or crush tablet(s)
• do not use within 1 hour after taking an antacid or milk
• it may cause stomach discomfort, faintness and cramps
Stop use and ask a doctor if• you have rectal bleeding or no
bowel movement after using this product.
These could be signs of a serious condition.
• you need to use a laxative for more than 1 week
If pregnant or breast-feeding,ask a health professional before use.

Keep out of reach of children.In case of overdose, get medical help or contact a Poison Control Center right away.

Directions

- take with a glass of water
- do not take more than directed
- adults and children 12 years and older: take 1 to 3 tablets in a single daily dose
- children 12 and under: ask a doctor

Other information

- store at controlled room temperature 20°-25°C (68°-77°F); excursions permitted between 15º-30ºC (59º-86ºF)
- avoid excessive humidity
- package not child resistant

Inactive ingredients

acacia, ammonium hydroxide,
calcium carbonate, corn starch, D&C yellow #10 lake,
FD&C yellow #6 lake, hypromellose, iron oxide black, lactose,
magnesium stearate, methylparaben, PEG, polydextrose,
polyvinyl acetate phthalate, propylparaben, propylene glycol,
povidone, shellac, simethicone, silica, sodium alginate,
sodium benzoate, sodium bicarbonate, stearic acid, sucrose,
talc, titanium dioxide, triacetin, triethyl citrate, wax.

Questions or comments?

1-800-540-3765